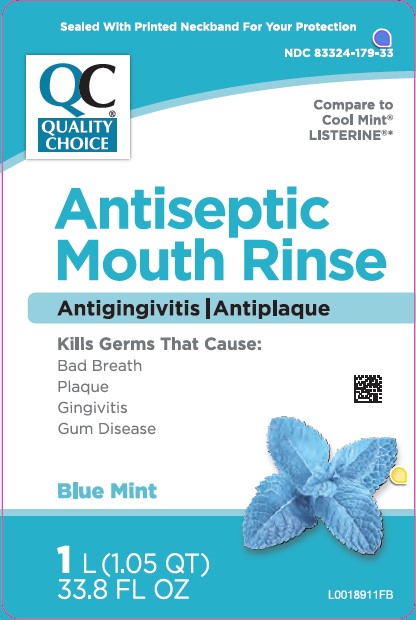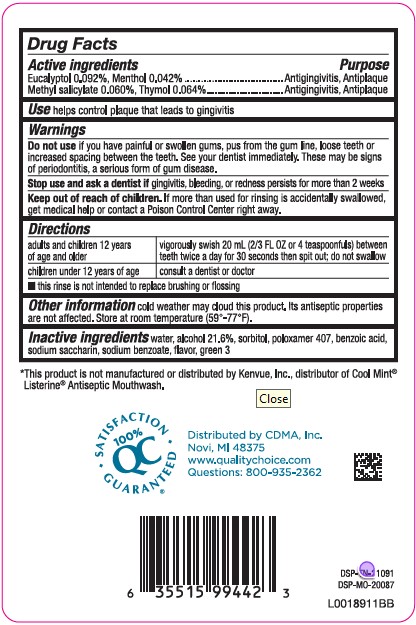 DRUG LABEL: Antiseptic Mouthrinse
NDC: 83324-179 | Form: MOUTHWASH
Manufacturer: Chain Drug Marketing Association
Category: otc | Type: HUMAN OTC DRUG LABEL
Date: 20260227

ACTIVE INGREDIENTS: EUCALYPTOL 0.92 mg/1 mL; MENTHOL 0.42 mg/1 mL; METHYL SALICYLATE 0.6 mg/1 mL; THYMOL 0.64 mg/1 mL
INACTIVE INGREDIENTS: ALCOHOL; WATER; SORBITOL; POLOXAMER 407; BENZOIC ACID; SACCHARIN SODIUM; SODIUM BENZOATE; FD&C GREEN NO. 3

Quality Choice 664.003/664AT rev 2 - 664AU
Blue Mint Antiseptic Mouthrinse

Active ingredients

Eucalyptol 0.092%

Menthol 0.042%

Methyl salicylate 0.060%

Thymol 0.064%

Purpose

Antigingivitis, Antiplaque

Use

helps control plaque that leads to gingivitis

Warnings

for this product

Do not use

if you have painful or swollen gums, pus from the gum line, loose teeth or increased spacing between the teeth. See your dentist immediately. These may be signs of periodontitis, a serious form of gum disease.

Stop use

and ask a dentist if gingivitis, bleeding, or redness persists for more than 2 weeks.

Keep out of reach of children.

If more than used for rinsing is accidentally swallowed, get medical help or contact a Poison Control Center right away.

Directions

adults and children 12 years of age and older - vigorously swish 20 mL (2/3 FL OZ or 4 teaspoonfuls) between teeth twice a day for 30 seconds then spit out; do not swallow

children under 12 years of age - consult a dentist or doctor

- this rinse is not intended to replace brushing or flossing

Other information

cold weather may cloud this product. Its antiseptic properties are not affected. Store at room temperature (59°-77°F)

Inactive ingredients

water, alcohol 21.6%, sorbitol, poloxamer 407, benzoic acid, sodium saccharin, sodium benzoate, flavor, green 3

Disclaimer

*This product is not manufactured or distributed by Kenvue, Inc., distributor of Cool Mint®Listerine® Antiseptic Mouthwash.

Adverse Reactions

QC 100% SATISFACTION GUARANTEED®

Distributed by CDMA, Inc.

Novi, MI 48376

www.qualitychoice.com

Questions: 800-935-2362

DSP-TN-21091

DSP-MO-20087

principal display panel

Sealed With Printed Neckband For Your Protection

NDC 83324-179-33

QC®

Quality

Choice

Compare to Cool Mint® LISTERINE®*

Antiseptic

Mouth Rinse

Antigingvitis/Antiplaque

Kills Germs That Cause:

Bad Breath

Plaque

Gingiviis

Gum Disease

BLUE MINT

1 L (1.05 QT) 33.8 FL OZ